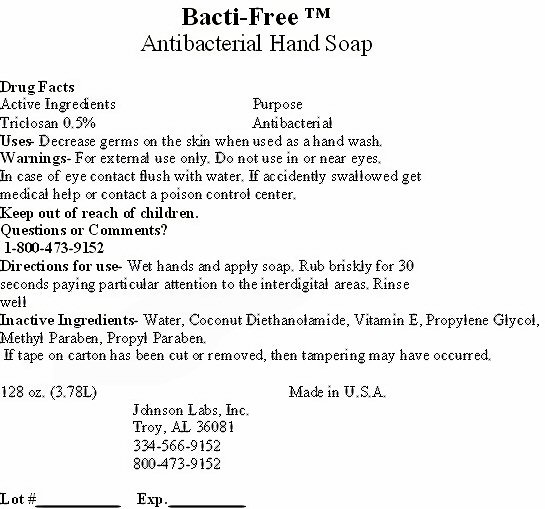 DRUG LABEL: Bacti-Free tm
NDC: 59854-300 | Form: LIQUID
Manufacturer: Johnson Labs, Inc.
Category: otc | Type: HUMAN OTC DRUG LABEL
Date: 20120402

ACTIVE INGREDIENTS: TRICLOSAN 0.0189 L/3.78 L
INACTIVE INGREDIENTS: WATER; COCO DIETHANOLAMIDE; ALPHA-TOCOPHEROL; PROPYLENE GLYCOL; METHYLPARABEN; PROPYLPARABEN

Active Ingredient

Drug facts

Active Ingredients Triclosan 0.5%

Purpose

Purpose Antibacterial

Keep Out Of Reach Of Children

Uses

Uses: Decrease germs on the skin when used as a hand wash.

Warnings

Warnings: For external use only. Do not use in or near the eyes. In case of eye contact flush with water. if accidently swallowed get medical help or contact a poison control center.

Directions for use - Wet hands and apply soap. Rub briskly for 30 seconds paying particular attention to the interdigital areas. Rinse well

Inactive Ingredients

Inactive Ingredients - Water, Coconut Diethanolamide, Vitamin E, Propylene Glycol, Methyl Paraben, Propyl Paraben.

Questions or Comments?

1-800-473-9152

Bacti-Free tm Label

Bacti-Free tm Antibacterial Hand Soap

If tape on carton has been cut or removed, then tampering may have occurred.

128 oz. (3.78L) Made in the u.S.A.

Johnson Labs, Inc. Troy, AL 36081 334-566-9152 800-473-9152

Lot # _____________________ Exp. ____________________